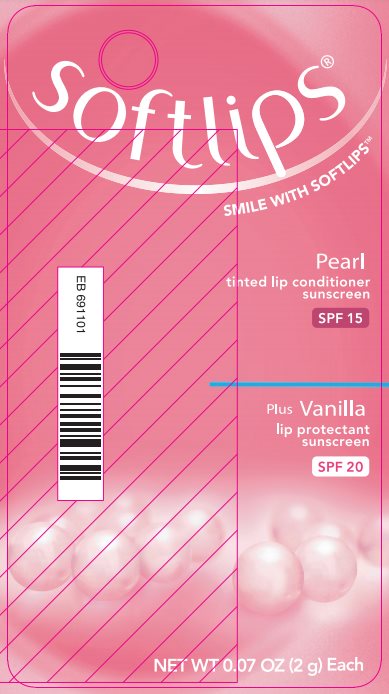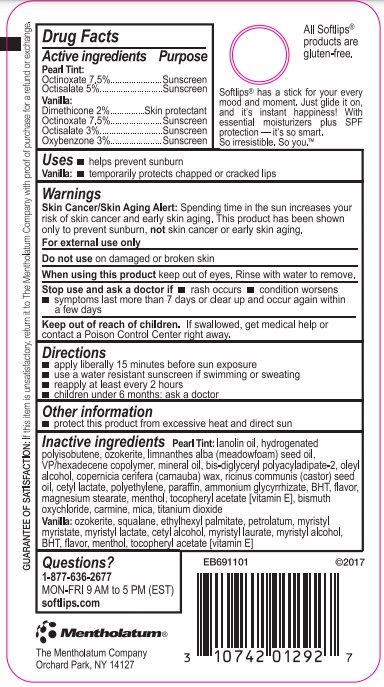 DRUG LABEL: Softlips
NDC: 10742-7011 | Form: KIT | Route: TOPICAL
Manufacturer: The Mentholatum Company
Category: otc | Type: HUMAN OTC DRUG LABEL
Date: 20241217

ACTIVE INGREDIENTS: OCTINOXATE 75 mg/1 g; OCTISALATE 50 mg/1 g; DIMETHICONE 20 mg/1 g; OCTINOXATE 75 mg/1 g; OCTISALATE 30 mg/1 g; OXYBENZONE 30 mg/1 g
INACTIVE INGREDIENTS: LANOLIN OIL; HYDROGENATED POLYBUTENE (1300 MW); CERESIN; MEADOWFOAM SEED OIL; VINYLPYRROLIDONE/HEXADECENE COPOLYMER; MINERAL OIL; BIS-DIGLYCERYL POLYACYLADIPATE-2; OLEYL ALCOHOL; CARNAUBA WAX; CASTOR OIL; CETYL LACTATE; PARAFFIN; AMMONIUM GLYCYRRHIZATE; BUTYLATED HYDROXYTOLUENE; MAGNESIUM STEARATE; MENTHOL, UNSPECIFIED FORM; .ALPHA.-TOCOPHEROL; BISMUTH OXYCHLORIDE; CARMINIC ACID; MICA; TITANIUM DIOXIDE; CERESIN; SQUALANE; ETHYLHEXYL PALMITATE; PETROLATUM; MYRISTYL MYRISTATE; MYRISTYL LACTATE; CETYL ALCOHOL; MYRISTYL LAURATE; MYRISTYL ALCOHOL; BUTYLATED HYDROXYTOLUENE; MENTHOL, UNSPECIFIED FORM; .ALPHA.-TOCOPHEROL

SOFTLIPS PEARL PLUS VANILLA

Softlips Pearl

Drug Facts

Active ingredient

Octinoxate 7.5%

Octisalate 5%

Purpose

Octinoxate – Sunscreen

Octisalate - Sunscreen

Uses

- helps prevent sunburn

Warnings

Skin Cancer/Skin Agent Alert: Spending time in the sun increases your risk of skin cancer and early skin aging. This product has been shown only to prevent sunburn, not skin cancer or early skin aging.

For external use only

Do Not Use

on damaged or broken skin

When Using

this product keep out of eyes. Rinse with water to remove.

Stop use and ask a doctor if

- rash occurs
- condition worsens
- symptoms last more than 7 days or clear up and occur again within a few days

Keep out of reach of children. If swallowed, get medical help or contact a Poison Control Center right away.

Dosage and Administration

- apply liberally 15 minutes before sun exposure
- use a water resistant sunscreen if swimming or sweating
- reapply at least every 2 hours
- children under 6 months: ask a doctor

Other information

- protect this product from excessive heat and direct sun

Inactive ingredients

lanolin oil, hydrogenated polyisobutene, ozokerite, limnanthes alba (meadowfoam) seed oil, VP/hexadecane copolymer, mineral oil, bis-diglycerl polyacyladipate-2, oleyl alcohol, copernicia cerifera (carnauba) wax, ricinus communis (castor) seed oil, cetyl lactate, polyethylene, paraffin, ammonium glycyrrhizate, BHT, flavor, magnesium stearate, menthol, tocopheryl acetate [vitamin E], bismuth oxychloride, carmine, mica, titanium dioxide

Questions or comments?

1-877-636-2677 MON-FRI 9 AM to 5 PM (EST)

Softlips.com

Softlips Vanilla

Drug Facts

Active Ingredient

Dimethicone 2%

Octinoxate 7.5%

Octisalate 3%

Oxybenzone 3%

Purpose

Dimethicone – Skin protectant

Octinoxate – Sunscreen

Octisalate – Sunscreen

Oxybenzone - Sunscreen

Uses

- helps prevent sunburn
- temporarily protects chapped or cracked lips

Warnings

Skin Cancer/Skin Agent Alert: Spending time in the sun increases your risk of skin cancer and early skin aging. This product has been shown only to prevent sunburn, not skin cancer or early skin aging.

For external use only

Do not use

on damaged or broken skin

When using this product

keep out of eyes. Rinse with water to remove.

Stop use and ask a doctor if

- rash occurs
- condition worsens
- symptoms last more than 7 days or clear up and occur again within a few days

Keep out of reach of children. If swallowed, get medical help or contact a Poison Control Center right away.

Dosage and Administration

- apply liberally 15 minutes before sun exposure
- use a water resistant sunscreen if swimming or sweating
- reapply at least every 2 hours
- children under 6 months: ask a doctor

Other information

- protect this product from excessive heat and direct sun

Inactive ingredients

ozokerite, squalane, ethylhexyl palmitate, petrolatum, myristyl myristate, myristyl lactate, cetyl alcohol, myristyl laurate, myristyl alcohol, BHT, flavor, menthol, tocopheryl acetate [vitamin E]

Questions or comments?

1-877-636-2677 MON-FRI 9 AM to 5 PM (EST)

Softlips.com